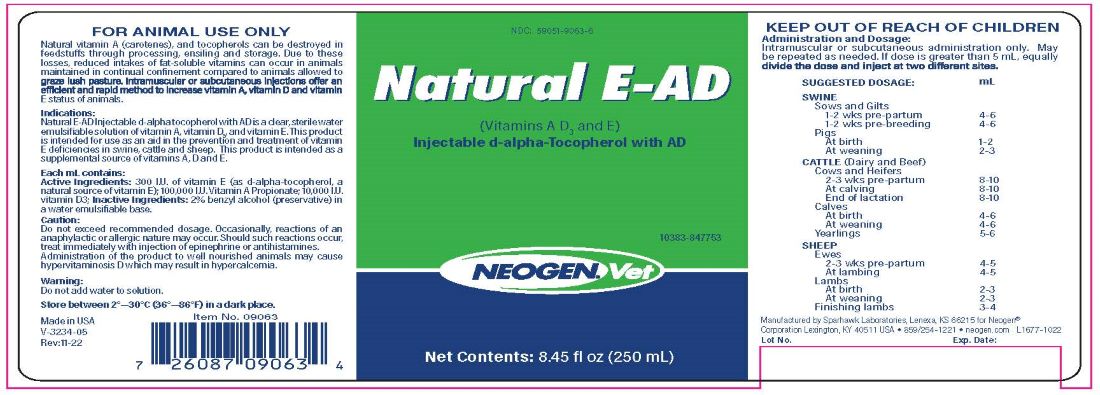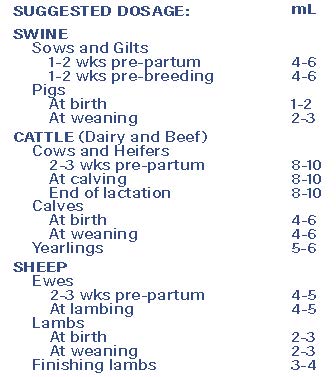 DRUG LABEL: Natural E-AD
NDC: 59051-9063 | Form: INJECTION
Manufacturer: Neogen Corporation - Nandino
Category: animal | Type: OTC ANIMAL DRUG LABEL
Date: 20231208

ACTIVE INGREDIENTS: .ALPHA.-TOCOPHEROL, D- 201 mg/1 mL; VITAMIN A 3.6 mg/1 mL; VITAMIN D 2.5 mg/1 mL

Natural E-AD

INDICATIONS AND USAGE

NATURAL E-AD

(Vitamin A, D3, and E)

Injectable d-alpha-tocopherol with AD

FOR ANIMAL USE ONLY

KEEP OUT OF REACH OF CHILDREN

Natural vitamin A (carotenes), and tocopherols can be destroyed in feedstuffs through processing, ensiling and storage. Due to these losses, reduced intakes of fat-soluble vitamins can occur in animals maintained in continual confinement compared to animals allowed to graze in lush pasture. Intramuscular or subcutaneous injections offer an efficient and rapid method to increase vitamin A, vitamin D and Vitamin E status of animals.

Indications:

Natural E-AD Injectable d-alpha tocopherol with AD is a clear, sterile water emulsifiablesolutionofvitaminA,vitaminD3,andvitaminE.Thisproduct is intended for use as an aid in the prevention and treatment of vitamin E deficiencies in swine, cattle and sheep. This product is intended as a supplemental source of vitamins A, D and E.

Each mL contains:

Active Ingredients: 300 I.U. of vitamin E (as d-alpha-tocopherol, a natural source of vitamin E); 100,000 I.U. Vitamin A Propionate; 10,000 I.U. vitamin D3; Inactive Ingredients: 2% benzyl alcohol (preservative) in a water emulsifiable base.

Caution:

Do not exceed recommended dosage. Occasionally, reactions of an anaphylactic or allergic nature may occur. Should such reactions occur, treat immediately with injection of epinephrine or antihistamines. Administration of the product to well nourished animals may cause hypervitaminosis D which may result in hypercalcemia.

Warning:

Do not add water to solution.

KEEP OUT OF REACH OF CHILDREN

STORAGE AND HANDLING

Store between 2°—30°C (36°—86°F) in a dark place

Administration and Dosage:

Intramuscular or subcutaneous administration only. May be repeated as needed. If dose is greater than 5 mL, equally divide the dose and inject at two different sites.